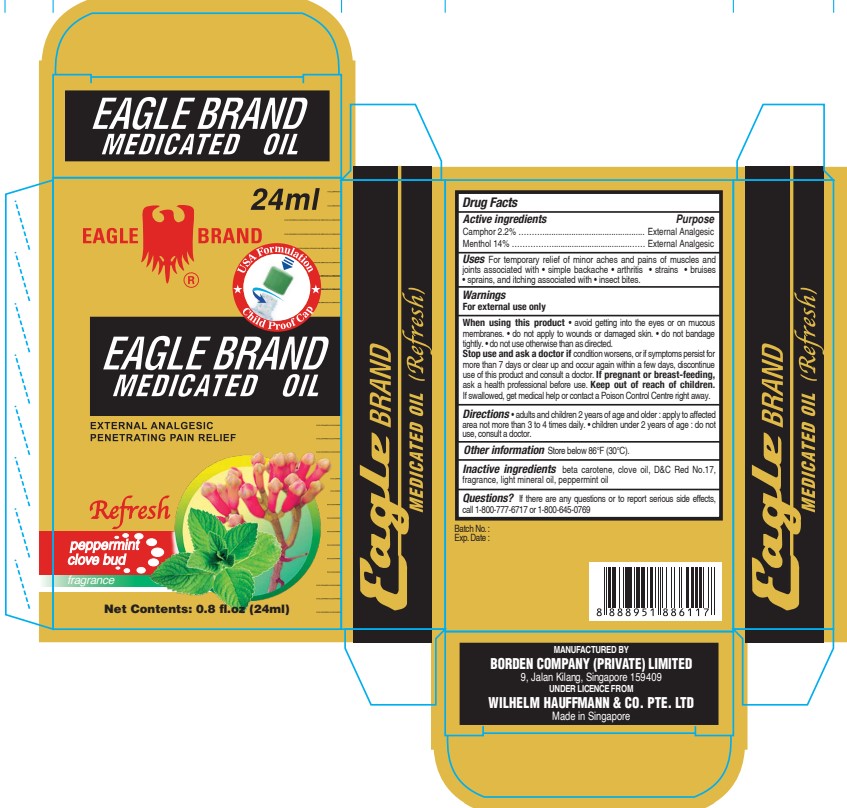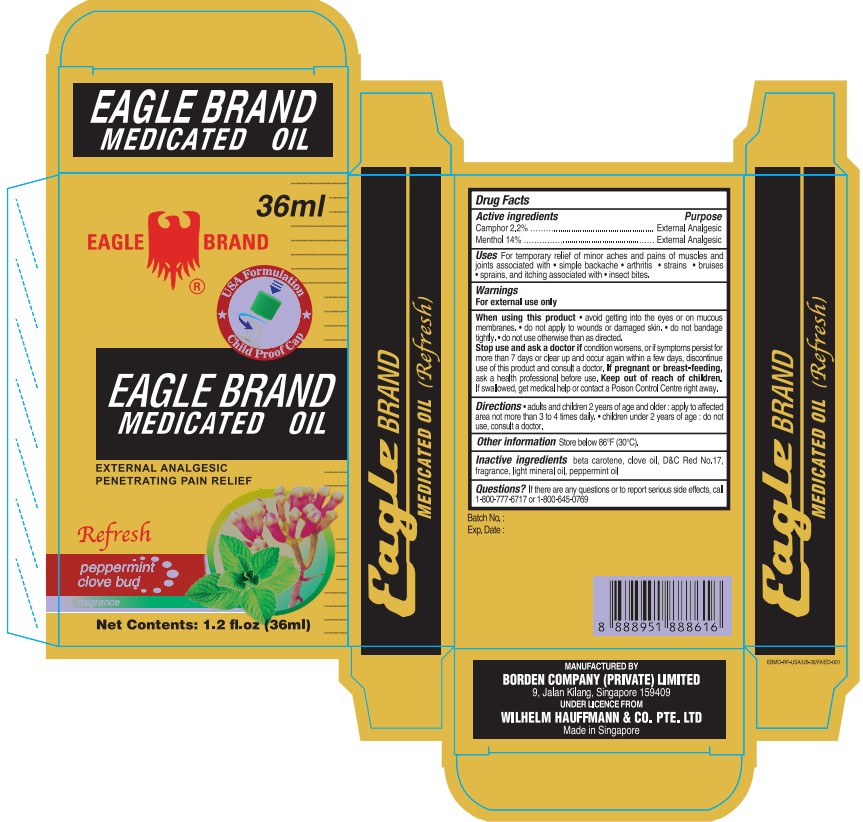 DRUG LABEL: Eagle Brand
NDC: 43405-013 | Form: OIL
Manufacturer: Borden Company (Private) Limited
Category: otc | Type: HUMAN OTC DRUG LABEL
Date: 20240819

ACTIVE INGREDIENTS: MENTHOL 14 g/100 mL; CAMPHOR (SYNTHETIC) 2.2 g/100 mL
INACTIVE INGREDIENTS: CLOVE OIL; LIGHT MINERAL OIL; PEPPERMINT OIL; BETA CAROTENE; D&C RED NO. 17

Eagle Brand Medicated Oil Refresh

Active ingredients

- Camphor 2.2%
- Menthol 14%

Purpose

External Analgesic

Uses

For temporary relief of minor aches and pains of muscles and joints associated with • simple backache • arthritis • strains • bruises • sprains, and itching associated with • insect bites.

Warnings

For external use only

When using this product

• Avoid getting into the eyes or on mucous membranes.

• Do not apply to wounds or damaged skin.

• Do not bandage tightly.

• Do not use otherwise than as directed.

Stop use and ask a doctor if

Condition worsens, or if symptoms persist for more than 7 days or clear up and occur again within a few days, discontinue use of this product and consult a doctor.

If pregnant or breast-feeding

Ask a health professional before use.

Keep out of reach of children

If swallowed, get medical help or contact a Poison Control Centre right away.

Directions

• Adults and children 2 years of age and older: apply to affected area not more than 3 to 4 times daily.
• Children under 2 years of age: do not use, consult a doctor.

Other information

Store below 86oF (30oC).

Inactive ingredients

beta carotene, clove oil, D&C Red No.17, fragrance, light mineral oil, peppermint oil

Questions?

If there are any questions or to report serious side effects, call 1-800-777-6717 or 1-800-645-0769.

Package Label

24ml NDC: 43405-013-24

36ml NDC: 43405-013-36